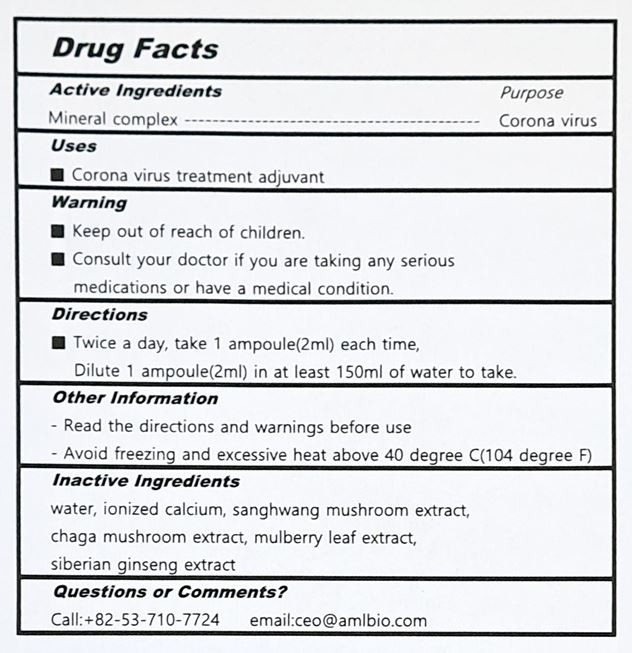 DRUG LABEL: Redu mineral
NDC: 81016-0005 | Form: LIQUID
Manufacturer: AML Bio Co., Ltd.
Category: otc | Type: HUMAN OTC DRUG LABEL
Date: 20240123

ACTIVE INGREDIENTS: WATER 100 g/100 mL
INACTIVE INGREDIENTS: ATORVASTATIN CALCIUM ANHYDROUS

Drug Facts

ACTIVE INGREDIENT

mineral complex

PURPOSE

corona virus

KEEP OUT OF REACH OF THE CHILDREN

INDICATIONS AND USAGE

Take 3 times a day, 3cc at a time

WARNINGS

■ For external use only.

■ Do not use in eyes.

■ lf swallowed, get medical help promptly.

■ Stop use, ask doctor lf irritation occurs.

■ Keep out of reach of children.

DOSAGE AND ADMINISTRATION

for external use only

INACTIVE INGREDIENT

Water